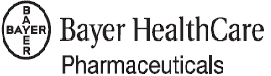 DRUG LABEL: Unknown
Manufacturer: Bayer HealthCare Pharmaceuticals Inc.
Category: prescription | Type: Human prescription drug label
Date: 20080310

Feridex I.V.
(ferumoxides injectable solution)

DESCRIPTION

Feridex I.V.® (ferumoxides injectable solution) is a sterile aqueous colloid of superparamagnetic iron oxide associated with dextran for intravenous (i.v.) administration as a magnetic resonance imaging contrast media. Chemically, ferumoxides is a non-stoichiometric magnetite, of average formula FeO1.44. Each milliliter of Feridex I.V. contains 11.2 milligrams of iron and 61.3 milligrams of mannitol at a pH of 5 to 9. The formulation also contains dextran (5.6– 9.1 mg/mL) and citrate (0.25–0.53 mg/mL). The osmolality is approximately 340 mOsm/kg; specific gravity is 1.04. Feridex I.V. is a black to reddish-brown aqueous colloid.

CLINICAL PHARMACOLOGY

General:

Feridex I.V. is an intravenously injected colloidal superparamagnetic iron oxide associated with dextran. It is a magnetic resonance imaging (MRI) contrast agent and is taken up by cells of the reticuloendothelial system (RES).

Pharmacokinetics:

Three healthy, adult male volunteers received a dose of Feridex I.V. 0.56 mg of Fe/kg (diluted in 100 mL of 5% dextrose and intravenously infused over 30 minutes). In these subjects, the mean ± SD peak serum iron concentration was 5.5 ± 0.6 μg/mL, elimination half-life was 2.4 ± 0.2 hours and total clearance 28.5 ± 1.6 mL/min. Feridex I.V. was completely cleared from the blood by 25 hours after administration. Less than 2% of the drug was excreted in the urine, as expected for iron.

At 24 hours, serum iron increased and the percent saturation of iron binding capacity decreased in a dose-dependent fashion. By 7 days, serum iron returned to pre-administration levels, and serum ferritin increased. These results are consistent with the iron in Feridex I.V. entering the usual iron metabolism cycle. Animal pharmacokinetics studies were consistent with these results in humans.

Imaging studies in rats showed a large decrease in liver signal intensity for the first 24 hours after dosing, followed by a gradual return to normal over 7 days. Radiotracer studies in rats were consistent with the iron in Feridex I.V. becoming part of the body iron pool. Histological studies in rats showed that the iron was in the RES and that it disappeared from the RES over 7 to 14 days with all evidence of iron gone by 14–28 days.

In human clinical studies, there was no difference in loss of signal intensity on images obtained between 0–3.5 hours after infusion. Loss of signal intensity decreased at 1 and 2 days.

Metabolism:

The iron in Feridex I.V. enters the normal body iron metabolism cycle as evidenced by transient increases in serum iron values one day after administration and increase in serum ferritin values 7 days after administration. The amount of iron contained in a single dose is 39 mg for a 70 kg individual. This is less than 1/5 the amount of iron contained in one unit of whole blood.

Special Populations:

Geriatric/Pediatric:

Pharmacokinetics in these populations were not studied. Patients enrolled in clinical trials were between 11 and 89 years old.

Gender:

Women showed a higher pre-contrast signal intensity and hence a larger decrease in liver signal intensity in images. This is consistent with a lower baseline iron in women.

Race:

Differences due to race were not noted.

Renal Insufficiency:

Feridex I.V. is not renally cleared; no studies were performed in patients with renal insufficiency.

Hepatic Insufficiency:

Patients with cirrhosis had less of a decrease in liver signal intensity than other patients with known or suspected liver lesions. Patients with cirrhosis also had a higher incidence of back pain. (See ADVERSE REACTIONS section.)

Hemochromatosis:

Individuals with iron overload were not studied. Feridex I.V. contains iron. Literature reports suggested that Feridex I.V. will not add information to their MRI evaluations, since iron overload causes loss in liver signal intensity.

Drug-Drug Interactions

In rats, the simultaneous administration of heparin was found to prolong the half-life of Feridex I.V. in the blood. The effects of Feridex I.V. administration on heparin anticoagulation are not known.

Pharmacodynamics:

Feridex I.V. shortens the relaxation times for nearby hydrogen atoms and reduces signal intensity in normal tissues. This results in signal loss (image darkening) on mid T1/T2 or strongly T2-weighted images. Tissues with decreased RES function (e.g., metastases, primary liver cancer, cysts and various benign tumors, adenomas, and hyperplasia) retain their native signal intensity, so the contrast between normal and abnormal tissue is increased.

CLINICAL TRIALS

Two clinical studies evaluated a total of 211 patients,(107 men and 104 women, 22–83 years of age) with a variety of known or suspected liver lesions. Of these patients, efficacy evaluations were completed on 96 patients in Study A, and 112 patients in Study B. At baseline, patients had a CECT (contrast enhanced computerized tomography) scan with any iodinated contrast agent and a noncontrast MRI (magnetic resonance imaging) within 24 hours before Feridex I.V. administration. Feridex I.V. (0.56 mg/kg) was administered intravenously over 30 minutes. Images were acquired up to 3.5 hours after the end of the infusion. The CECT, unenhanced MRI, and Feridex I.V. enhanced MRI images were read blindly (i.e., by radiologists who were not told of the patient's medical history or the presence of image contrast enhancing drugs). Results from blindly read images were compared to the final clinical diagnosis. The final clinical diagnoses were confirmed with histopathologic, surgical, or biopsy findings in 86 (41%) of patients. MRI scans were evaluated for the quantitative analysis of signal intensity in liver lesion(s), and by blinded evaluations of the resulting images for changes in number and location of lesions, delineation of lesion margins, presence or absence of lesions, and characterization of lesions.

Based upon these two studies, Feridex I.V. reduced the signal intensity of normal liver on T2 weighted pulse sequences to improve MRI contrast. Contrast to noise ratios were increased on T2 images and decreased on T1 images. Image interpretations for contrast enhancement, the number of lesions identified, and the sensitivity and specificity of the determination of whether an abnormal lesion was present are shown in the following table. The mean number of lesions seen before and after Feridex I.V. were comparable. The majority of new lesions (86%) were 0.5 cm–1.0 cm in size, but other lesions were seen that were <0.5 cm or >1.0 cm.

IMAGE INTERPRETATION RESULTS AFTER UNENHANCED MRI, CECT [MRI (magnetic resonance image), CECT (contrast enhanced computerized tomography)] AND
FERIDEX I.V. ENHANCED MRI IN TWO CLINICAL STUDIES OF PATIENTS WITH
KNOWN OR SUSPECTED LIVER LESIONS
Outcome Measure | Control Comparisons | Study A; (N = 96) | Study B; (N=112)
Contrast between normal and; abnormal liver tissue seen on MRI | MRI Contrast Better with Feridex I.V.; MRI Contrast Same with Feridex I.V.; MRI Contrast Worse with Feridex I.V. | 84%; 13%; 3%; (p<0.01) | 86%; 12%; 2%; (p<0.01)
Number of Patients with Lesions; Seen on MRI | Patients with:; More before Feridex I.V.; Same before and after Feridex I.V.; More After Feridex I.V | 13%; 62%; 25% | 21%; 51%; 28%
Number of liver lesions seen on MRI; (Mean ± SD) | MRI before Feridex I.V.; after Feridex I.V. | 7.3 ± 15.9; 6.7 ± 10.4; (p=n.s.) | 6.7 ± 14.8; 7.3 ± 15.5; (p=n.s.)
Sensitivity/specificity for the; detection of abnormal liver lesions | MRI before Feridex I.V. vs. Final diagnosis: [Final diagnosis: e.g., by biopsy, surgical resection, autopsy, MRI procedures other than with Feridex I.V., CECT, ultrasound, or other clinical information.]; Sensitivity; Specificity | 91%; 71% | 92%; 77%
Sensitivity/specificity for the; detection of abnormal liver lesions | MRI after Feridex I.V. vs. Final diagnosis:; Sensitivity; Specificity | 95%; 76% | 92%; 85%
Sensitivity/specificity for the; detection of abnormal liver lesions | CECT vs. Final diagnosis:; Sensitivity; Specificity | 96%; 67% | 98%; 58%

In various types of liver lesions, Feridex I.V. caused a smaller decrease in the signal intensity (59%–105% of the unenhanced) than in the surrounding liver (28%–41% of the unenhanced). The signal intensity changes are not characterized sufficiently to support distinguishing between types of lesions or diseases. Whether patients with cirrhosis have similar changes in signal intensity is not known.

PERCENT DECREASE IN MRI SIGNAL INTENSITY (SI) ON T2 IMAGES AFTER
FERIDEX I.V.
Disease State | Surrounding Liver |  | Lesion in Question
Disease State | N | % decrease in SI; after Feridex I.V. | N | % decrease in SI; after Feridex I.V.
Patients with benign, malignant,; hepatocellular and non-hepatocellular; lesions (excluding cirrhosis) | 162 | 59–72% | 153 | 0–41%

Imaging of the spleen by Feridex I.V. has not been adequately studied.

INDICATIONS AND USAGE

Feridex I.V. is indicated for I.V. administration as an adjunct to MRI (in adult patients) to enhance the T2 weighted images used in the detection and evaluation of lesions of the liver that are associated with an alteration in the RES.

CONTRAINDICATIONS

Feridex I.V. is contraindicated in patients with known allergic or hypersensitivity reactions to parenteral iron, parenteral dextran, parenteral iron-dextran, or parenteral iron-polysaccharide preparations.

WARNINGS

Anaphylactic-like reactions and hypotension have been noted in some patients receiving Feridex I.V., other iron and dextran containing formulations, or radiographic contrast media. In clinical trials, anaphylactic and allergic adverse events occurred in 11/2240 (0.5%) of the patients who received Feridex I.V. These events include dyspnea, other respiratory symptoms, angioedema, generalized urticaria, and hypotension; and required treatment.

Acute severe back, leg or groin pain occurred in some patients. In clinical trials, 55/2240 (2.5%) of the patients experienced pain that was severe enough to cause interruption or discontinuation of the infusion. In most patients, the symptoms developed within 1 to 15 minutes (up to 45 minutes). Some patients required treatment with corticosteroids, intravenous fluids or muscle relaxants. Pain may occur alone or with other symptoms such as hypotension and dyspnea. Patients with both pain and allergic symptoms received treatment with a combination of medications directed toward each event. (See ADVERSE REACTIONS section.)

Patients with autoimmune disease have not been studied with Feridex I.V., but have been reported in published literature to have a high rate of adverse reactions to injectable iron formulations.

If hypersensitivity, or moderate to severe pain occurs, the injection should be stopped, and symptomatic treatment should be given.

A fully equipped emergency cart, or equivalent supplies and equipment, and personnel competent in recognizing and treating anaphylactic or anaphylactoid reactions should be available.

PRECAUTIONS

GENERAL:

THE DECISION TO USE CONTRAST ENHANCEMENT SHOULD INCLUDE A CONSIDERATION OF THE RISK OF THE DRUG, THE RISK OF THE PROCEDURE, THE EXPECTED BENEFIT OF THE IMAGE AND THE PATIENT'S UNDERLYING DISORDER. THE DECISION TO USE FERIDEX I.V. SHOULD BE BASED UPON CAREFUL EVALUATION OF CLINICAL DATA, OTHER RADIOLOGIC DATA, AND THE RESULTS OF UNENHANCED MRI.

Patients receiving contrast agents and especially those who are medically unstable must be closely supervised. Diagnostic procedures which involve the use of any contrast agent should be carried out under the direction of personnel with the prerequisite training and with a thorough knowledge of the particular procedure to be performed.

After parenteral administration of a contrast agent, competent personnel, a fully equipped emergency cart or equivalent, and emergency facilities should be available for at least 60 to 120 minutes.

Immunologic Reactions:

The possibility of a reaction including serious, life-threatening, fatal, anaphylactoid or cardiovascular reactions should always be considered. Increased risk is associated with a known sensitivity to iron or dextran, history of previous reaction to a radiographic contrast agent, known allergies, other hypersensitivities, and underlying immune disorders, autoimmunity or immunodeficiencies that predispose to specific or non specific mediator release.

Skin testing cannot be relied upon to predict severe reactions and skin testing may itself be hazardous to the patient. A thorough medical history with emphasis on allergy and hypersensitivity, immune, autoimmune and immunodeficiency disorders, and prior receipt of and response to the injection of any contrast agent, may be more accurate than pretesting in predicting potential adverse reactions.

Feridex I.V., which contains iron, should be used with caution in patients with disorders associated with iron over load (e.g., hemosiderosis, chronic hemolytic anemia with frequent blood transfusions).

Extreme caution during injection of a contrast agent is necessary to avoid extravasation. This is especially important in patients with severe arterial or venous disease.

Repeat Procedures:

If the physician determines that imaging needs to be repeated, based on the pharmacodynamics of Feridex I.V., repeat images could be obtained up to 3.5 hours after the original infusion without re-injection. Data on timing for and safety of repeated injections are not available. (See CLINICAL PHARMACOLOGY section.)

Information for Patients

Patients receiving Feridex I.V. should be instructed to inform their physician or health care provider:

1. If you are pregnant or nursing. (See PRECAUTIONS—PREGNANCY—Teratogenic Effects. — Pregnancy Category C section.)
2. If you are allergic to iron or dextran containing drugs or if you had any reactions to previous injections of dyes used for x-ray procedures. Also, inform your physician or health care provider if you are allergic to any other drugs or food, or if you have immune, autoimmune or immune deficiency disorders. (See PRECAUTIONS—GENERAL: section.)
3. About all medications you are currently taking, including non-prescription (over-the-counter) drugs and vitamins, before you have this procedure.

Patients should be informed that:

1. Feridex I.V. has been prescribed for liver enhancement during MRI.
2. Feridex I.V. may cause severe back, groin, leg, or other pain, or allergic reactions.
3. The infusion fluid is a dark color.
4. The skin surrounding the infusion site may discolor if there is extravasation. The discoloration should disappear over time.

Drug Interactions

Drug interactions were not noted and were not studied in clinical studies. (See CLINICAL PHARMACOLOGY section on Drug-Drug Interactions.)

Feridex I.V. administration provides elemental iron. In patients who are receiving supplemental iron orally or parenterally, the dose of supplemental iron may need to be decreased.

The effect of concomitant parenteral iron on Feridex I.V. dosing is not known. (See CLINICAL PHARMACOLOGY section.)

LABORATORY TEST FINDINGS

Serum iron levels may be above the normal range following Feridex I.V. administration. Transient increases in serum iron of 15-100% of baseline were observed 18 to 24 hours after Feridex I.V. administration, and returned to normal in most patients by 7 days after administration. Increases in serum ferritin levels were seen 1 to 7 days after administration.

(See CLINICAL PHARMACOLOGY, Pharmacokinetics: section.)

In a Phase 1 study in normal subjects, PTT was statistically significantly increased; however, all values were within the normal range and no subjects had a more than 40% increase from baseline. In clinical trials of patients who had baseline hematologic abnormalities associated with underlying liver disease, an effect of Feridex I.V. on platelet or PTT was not demonstrated.

In patients with low hematocrit and hemoglobin, over a period of 48 hours to 7 days after Feridex I.V., the serum iron, the hematocrit and hemoglobin levels increase slightly.

CARCINOGENESIS, MUTAGENESIS, AND IMPAIRMENT OF FERTILITY

Long term studies in animals have not been performed to evaluate the carcinogenic potential of Feridex I.V. Therapeutic iron dextran products have been associated with the development of sarcomas at the intramuscular injection sites; the length of treatment or the length of time after injection until development of tumor is not known. Ferumoxides are iron oxides associated with dextran. Whether Feridex I.V. has a risk of tumorigenesis that is similar to that of iron dextran is not known.

Feridex I.V. was not genotoxic in a series of studies that included the Ames test, the CHO/HGPRT forward mutation assay, a chromosome aberration test in CHO cells, an unscheduled DNA synthesis assay, and a micronucleus assay in mice.

Feridex I. V. did not impair the fertility of male or female rats at dosages that were up to approximately 5 times the clinical dose when normalized to body surface area.

PREGNANCY

Teratogenic Effects.

Pregnancy Category C.

Feridex I.V. is teratogenic in rabbits at all studied doses. The smallest dose studied was approximately six times the clinical dose when normalized to body surface area. Adequate and well controlled studies were not conducted in pregnant women. Feridex I.V. should be used during pregnancy only if the potential benefit justifies the potential risk.

NURSING MOTHERS

It is not known whether Feridex I.V. is excreted in human milk. This drug should only be used in nursing women if the benefit clearly outweighs the risk.

PEDIATRIC USE

Safety and efficacy of Feridex I.V. in the pediatric population have not been established.

ADVERSE REACTIONS

In clinical trials, a total of 2240 subjects (32 healthy volunteers and 2208 patients with known or suspected liver lesions) received Feridex I.V. Of these subjects, 35% received the recommended dose of 0.56 mg Fe/kg and 62% received a dose of 0.84 mg Fe/kg. Forty-four percent were female and 56% were male, with a mean age of 54.9 years (range 11–89).

Of 866 subjects in whom race is known, 647 (75%) were Asian, 199 (22%) were Caucasian, 14 (2%) were Black, 3 (<1%) were Hispanic, and 3 (<1%) other. Racial demographic information was not available for the 1374 subjects in European clinical trials.

Of the 2240 subjects, 197 (8.8%) experienced an adverse event. The most commonly noted adverse experiences were back pain (3.4%), and vasodilation (2.3%).

In a subgroup of 1535 patients in controlled clinical trials, in 44 (2.9%) of the patients [9/226 (3.9%) in US, 10/635 (1.6%) in Japanese, and 25/674 (3.7%) in European studies] the infusion was interrupted or discontinued because of acute, moderate to severe pain (back, lower torso, chest, groin, or upper leg) with or without hypotension. Some patients required treatment. In a few of the patients with pain 11/44 (25%), the infusion was interrupted, restarted, and completed. (See WARNINGS section.)

Pain in any location was reported in 4.2% of these 1535 patients given Feridex I.V.

In a subgroup of 689 patients in whom associated underlying disorders were evaluated, back pain occurred in 18/144 (12.5%) patients with cirrhosis and in 10/545 (1.8%) patients who did not have cirrhosis. The frequency of pain in patients with other liver abnormalities is not known.

Anaphylactic and allergic adverse events (e.g., generalized urticaria, respiratory symptoms, and hypotension) that required acute treatment occurred in 11/2240 (0.5%) of patients who received Feridex I.V.

Most other adverse reactions were mild to moderate, of short duration, and resolved spontaneously without treatment. A relationship between adverse events and dose, age, or gender was not observed.

Adverse reactions that occurred in greater than or equal to 0.5% of the 1535 patients in controlled clinical trials are listed below in related categories, in decreasing order of occurrence within each system, and regardless of causality:

ADVERSE EVENTS IN ≥0.5% OF THE 1535 PATIENTS IN CONTROLLED CLINICAL
TRIALS WITH FERIDEX I.V.
Categories | Adverse Event | Number of; Patients (%)
Number of patients who received; Feridex I.V. |  | 1535
Number of patients with any; adverse event |  | 144 (9.4%)
Digestive System | Nausea | 11 (0.7%)
Body as a whole | Total (pain all sources); Pain Back/Leg/Pain Leg; Headache; Pain Chest | 65 (4.2%); 56 (3.6%); 13 (0.8%); 10 (0.7%)
Hypersensitivity | Total (hypersensitivity all sources); Vasodilation; Urticaria/Erythematous Rash/Rash; Dyspnea | 53 (3.4%); 33 (2.1%); 12 (0.7%); 8 (0.5%)

The following adverse reactions were observed in <0.5% of the subjects receiving Feridex I.V.: DIGESTIVE: diarrhea, vomiting, anorexia; BODY PAIN: pain abdomen, pain neck, fatigue, fever; CARDIOVASCULAR: hypertension, hypotension, arrhythmias; NERVOUS: dizziness, paresthesia; SKIN AND APPENDAGES: pruritus, sweating; SPECIAL SENSES: abnormal vision, taste perversion; RESPIRATORY: cough, epistaxis, rhinitis.

(See sections on CONTRAINDICATIONS, WARNINGS and PRECAUTIONS.)

In 705 patients who received Feridex I.V. in other trials, similar adverse events were reported.

OVERDOSE

Overdose with Feridex I.V. has not been reported. Acute toxicity is apt to be related to iron overload, acute back pain and allergic events. Chronic administration of therapeutic iron dextran in excess of the total amount of iron needed for iron stores may lead to hemosiderosis.

A study of (59Fe) complexed iron-dextran utilizing isotonic saline in a 4-hour in vitro dialysis run indicated that less than 0.5% of the injected radio labeled iron dextran traversed the dialysis membrane. Feridex I.V. contains iron associated with dextran. Whether Feridex I.V. is dialyzable is not known.

DOSAGE AND ADMINISTRATION

Dose

The recommended dosage of Feridex I.V. is 0.56 milligrams of iron (0.05 mL Feridex I.V.) per kilogram of body weight, that is diluted in 100 mL of 5% dextrose solution and given over 30 minutes. (SeeDrug Preparation Section). The diluted drug is administered through a 5 micron filter at a rate of 2 to 4 milliliters per minute.

Feridex I.V. should not be administered undiluted.

Drug Preparation

1. The vial should be used at room temperature. Mix by inverting the vial 10 to 20 times.
2. Draw up the appropriate dose of Feridex I.V. into a sterile syringe.
3. Dilute Feridex I.V. by injecting it into 100 mL of 5% dextrose solution (D5W).
4. The bag should be inverted two or three times to assure dilution.
5. The drug product should be administered within 8 hours following dilution.

Imaging

Post-contrast imaging may begin immediately after the dose is infused and may be performed up to 3.5 hours after the end of the infusion. T2-weighted pulse sequences provide the maximum contrast effect.

HOW SUPPLIED

Feridex I.V. is black to reddish brown liquid containing 11.2 mg Fe/mL (56 mg of iron/vial) in a vial with a tear off seal. Feridex I.V. is supplied in 5 mL single dose vials in boxes of 1 (NDC 59338–7035–1) and 5 (NDC 59338–7035–5). An administration filter is supplied for each vial.

Feridex I.V. is stable for 24 hours after dilution.

STORAGE

Storage at 2–30 °C (35–86 °F). DO NOT FREEZE.

If there are indications that the package has been exposed to freezing, DO NOT USE.

Rx Only

The following patents have claims directed to the drug: U.S.P. 4,770,183, U.S.P. 4,827,945, U.S.P. 4,951,675, U.S.P. 5,055,288, U.S.P. 5,102,652, U.S.P. 5,219,554, U.S.P. 5,248,492

Manufactured for:

Bayer HealthCare Pharmaceuticals Inc. Wayne, NJ 07470

Manufactured by Advanced Magnetics, Inc., Cambridge, MA 02138

Feridex I.V. is a registered trademark of Advanced Magnetics, Inc.

© 2007, Bayer HealthCare Pharmaceuticals Inc. All rights reserved

Revised May 2007 Printed in USA 6700900/6102 REV 08